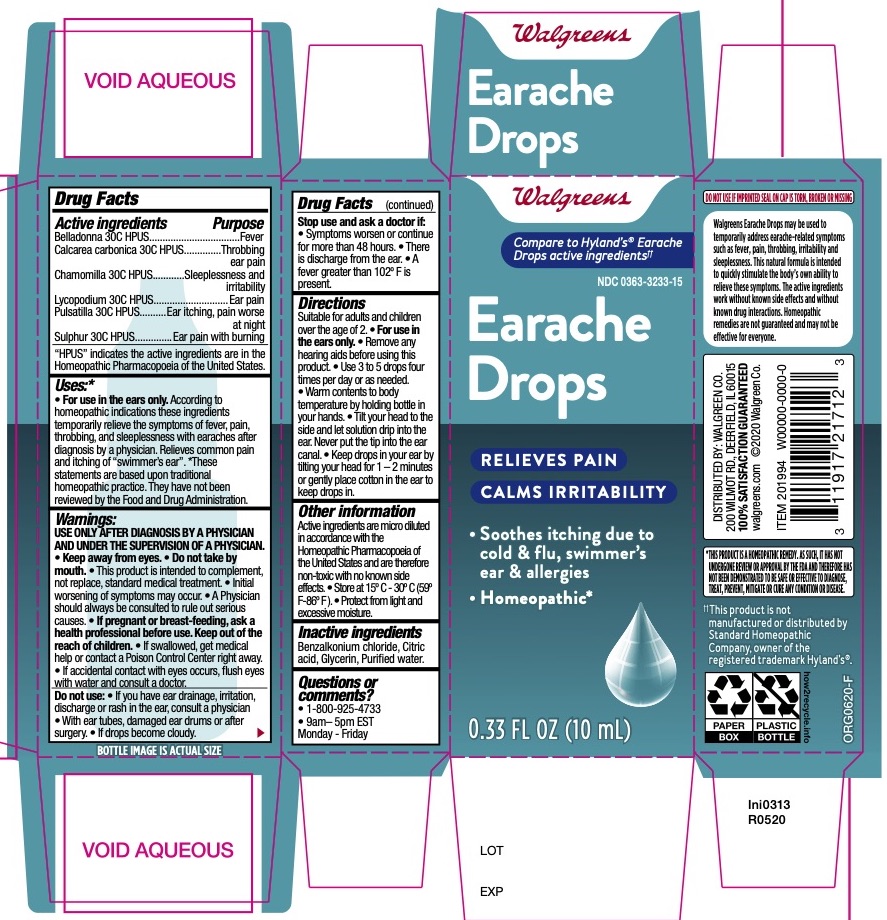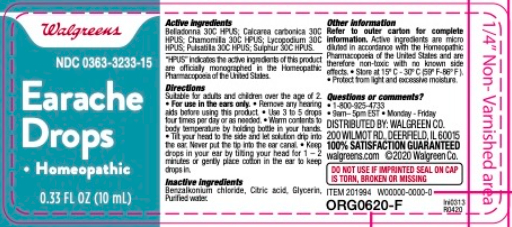 DRUG LABEL: WALGREENS EARACHE DROPS
NDC: 0363-3233 | Form: LIQUID
Manufacturer: Walgreen Company
Category: homeopathic | Type: HUMAN OTC DRUG LABEL
Date: 20251119

ACTIVE INGREDIENTS: BELLADONNA LEAF 30 [hp_C]/1 mL; CALCIUM CARBONATE 30 [hp_C]/1 mL; CHAMOMILE 30 [hp_C]/1 mL; LYCOPODIUM CLAVATUM SPORE 30 [hp_C]/1 mL; ANEMONE PATENS WHOLE 30 [hp_C]/1 mL; SULFUR 30 [hp_C]/1 mL
INACTIVE INGREDIENTS: CITRIC ACID MONOHYDRATE; WATER; BENZALKONIUM CHLORIDE; GLYCERIN

Walgreens Earache Drops

Drug Facts

Active ingredients | Purpose
Belladonna 30C HPUS | Fever
Calcarea Carbonica 30C HPUS | Throbbing ear pain
Chamomilla 30C HPUS | Sleeplessness and irritability
Lycopodium 30C HPUS | Ear pain
Pulsatilla 30C HPUS | Ear itching, pain worse at night
Sulphur 30C HPUS | Ear pain with burning

"HPUS" indicates that the active ingredients are in the official Homeopathic Pharmacopœia of the United States.

Purpose

Belladonna - Fever
Calcarea carbonica - Throbbing ear pain
Chamomilla - Sleeplessness and irritability
Lycopodium - Ear pain Pulsatilla - Ear itching, pain worse at night
Sulphur - Ear pain with burning

Uses

• For use in the ears only. According to homeopathic indications these ingredients temporarily relieve the symptoms of fever, pain, throbbing, and sleeplessness with earaches after diagnosis by a physician. Relieves common pain and itching of “swimmer’s ear”. *These statements are based upon traditional homeopathic practice. They have not been reviewed by the Food and Drug Administration.

Warnings

USE ONLY AFTER DIAGNOSIS BY A PHYSICIAN AND UNDER THE SUPERVISION OF A PHYSICIAN. • Keep away from eyes. • Do not take by mouth. • This product is intended to complement, not replace, standard medical treatment. • Initial worsening of symptoms may occur. • A Physician should always be consulted to rule out serious causes.

• If accidental contact with eyes occurs, flush eyes with water and consult a doctor.

PREGNANCY OR BREAST FEEDING

• If pregnant or breast-feeding, ask a health professional before use.

KEEP OUT OF REACH OF CHILDREN

Keep out of the reach of children. • If swallowed, get medical help or contact a Poison Control Center right away.

Do not use: • If you have ear drainage, irritation, discharge or rash in the ear, consult a physician • With ear tubes, damaged ear drums or after surgery. • If drops become cloudy.

Stop use and ask a doctor if:

• Symptoms worsen or continue for more than 48 hours. • There is discharge from the ear. • A fever greater than 102o F is present.

Directions

Suitable for adults and children overtheageof2.•Forusein the ears only. • Remove any hearing aids before using this product. • Use 3 to 5 drops four times per day or as needed.

• Warm contents to body temperature by holding bottle in your hands. • Tilt your head to the side and let solution drip into the ear. Never put the tip into the ear canal. • Keep drops in your ear by tilting your head for 1 – 2 minutes or gently place cotton in the ear to keep drops in.

Other information

Active ingredients are micro diluted in accordance with the Homeopathic Pharmacopoeia of the United States and are therefore non-toxic with no known side effects. • Store at 15o C - 30o C (59o F-86o F). • Protect from light and excessive moisture.

Inactive ingredients

Benzalkonium chloride, Citric acid, Glycerin, Purified water.

Questions or comments?

• 1-800-925-4733 • 9am– 5pm EST Monday - Friday